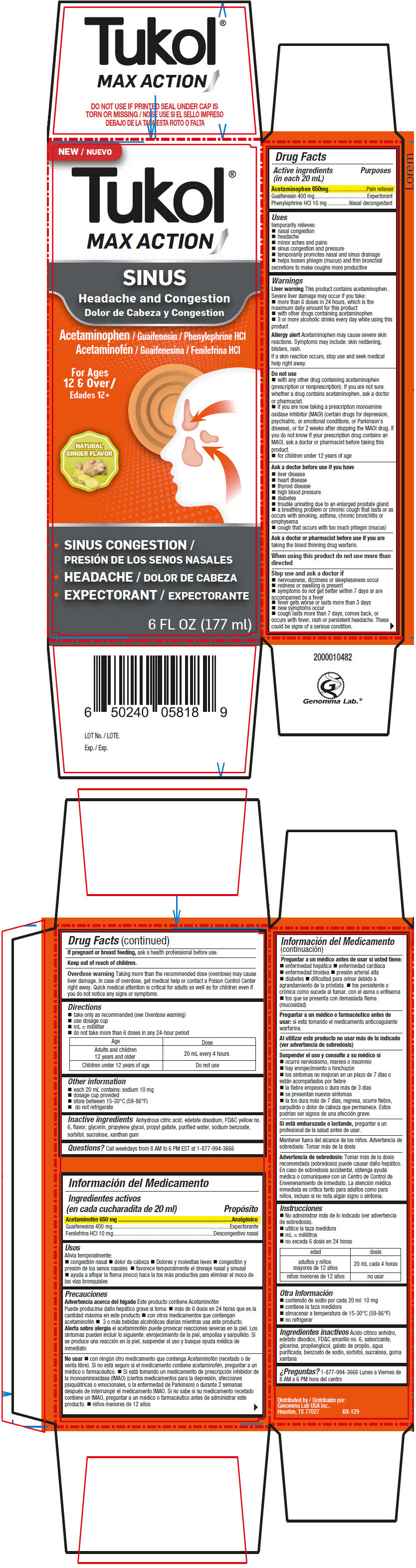 DRUG LABEL: Tukol Max Action Sinus Liquid
NDC: 50066-305 | Form: SYRUP
Manufacturer: Genomma Lab USA
Category: otc | Type: HUMAN OTC DRUG LABEL
Date: 20210803

ACTIVE INGREDIENTS: Acetaminophen 32.5 mg/1 mL; Guaifenesin 20 mg/1 mL; PHENYLEPHRINE HYDROCHLORIDE 0.5 mg/1 mL
INACTIVE INGREDIENTS: WATER; Glycerin; Propylene Glycol; Sorbitol; Sodium benzoate; Sucralose

Tukol® Max Action Sinus Liquid

Drug Facts

ACTIVE INGREDIENT

PURPOSE

Active ingredients (in each 20 mL) | Purposes
Acetaminophen 650mg | Pain reliever
Guaifenesin 400 mg | Expectorant
Phenylephrine HCl 10 mg | Nasal decongestant

Uses

temporarily relieves:

- nasal congestion
- headache
- minor aches and pains
- sinus congestion and pressure
- temporarily promotes nasal and sinus drainage
- helps loosen phlegm (mucus) and thin bronchial secretions to make coughs more productive

Warnings

Liver warning

This product contains acetaminophen.

Severe liver damage may occur if you take:

- more than 6 doses in 24 hours, which is the maximum daily amount for this product
- with other drugs containing acetaminophen
- 3 or more alcoholic drinks every day while using this product

Allergy alert

Acetaminophen may cause severe skin reactions. Symptoms may include: skin reddening, blisters, rash.

If a skin reaction occurs, stop use and seek medical help right away.

Do not use

- with any other drug containing acetaminophen (prescription or nonprescription). If you are not sure whether a drug contains acetaminophen, ask a doctor or pharmacist.
- if you are now taking a prescription monoamine oxidase inhibitor (MAOI) (certain drugs for depression, psychiatric, or emotional conditions, or Parkinson's disease), or for 2 weeks after stopping the MAOI drug. If you do not know if your prescription drug contains an MAOI, ask a doctor or pharmacist before taking this product.
- for children under 12 years of age

Ask a doctor before use if you have

- liver disease
- heart disease
- thyroid disease
- high blood pressure
- diabetes
- trouble urinating due to an enlarged prostate gland
- a breathing problem or chronic cough that lasts or as occurs with smoking, asthma, chronic bronchitis or emphysema
- cough that occurs with too much phlegm (mucus)

Ask a doctor or pharmacist before use if you are taking the blood thinning drug warfarin.

When using this product do not use more than directed

Stop use and ask a doctor if

- nervousness, dizziness or sleeplessness occur
- redness or swelling is present
- symptoms do not get better within 7 days or are accompanied by a fever
- fever gets worse or lasts more than 3 days
- new symptoms occur
- cough lasts more than 7 days, comes back, or occurs with fever, rash or persistent headache. These could be signs of a serious condition.

PREGNANCY OR BREAST FEEDING

If pregnant or breast feeding, ask a health professional before use.

Keep out of reach of children.

Overdose warning

Taking more than the recommended dose (overdose) may cause liver damage. In case of overdose, get medical help or contact a Poison Control Center right away. Quick medical attention is critical for adults as well as for children even if you do not notice any signs or symptoms.

Directions

- take only as recommended (see Overdose warning)
- use dosage cup
- mL = milliliter
- do not take more than 6 doses in any 24-hour period

Age | Dose
Adults and children 12 years and older | 20 mL every 4 hours
Children under 12 years of age | Do not use

Other information

- each 20 mL contains: sodium 10 mg
- dosage cup provided
- store between 15-30°C (59-86°F)
- do not refrigerate

Inactive ingredients

Anhydrous citric acid, edetate disodium, FD&C yellow no. 6, flavor, glycerin, propylene glycol, propyl gallate, purified water, sodium benzoate, sorbitol, sucralose, xanthan gum

Questions?

Call weekdays from 8 AM to 6 PM EST at 1-877-994-3666

Distributed by:
Genomma Lab USA Inc.,
Houston, TX 77027

PRINCIPAL DISPLAY PANEL - 177 ml Bottle Carton

NEW

Tukol®

MAX ACTION

SINUS

Headache and Congestion

Acetaminophen / Guaifenesin / Phenylephrine HCl

For Ages
12 & Over

NATURAL
GINGER FLAVOR

♦ SINUS CONGESTION
♦ HEADACHE
♦ EXPECTORANT

6 FL OZ (177 ml)